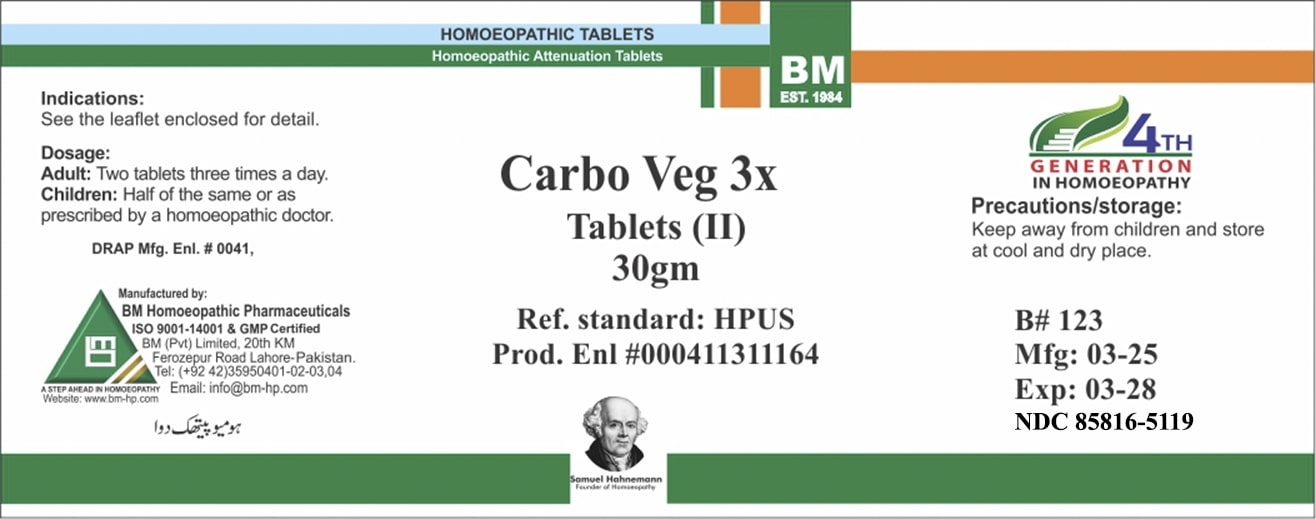 DRUG LABEL: BM Carbo Veg
NDC: 85816-5119 | Form: GLOBULE
Manufacturer: BM Private Limited
Category: homeopathic | Type: HUMAN OTC DRUG LABEL
Date: 20250630

ACTIVE INGREDIENTS: ACTIVATED CHARCOAL 3 [hp_X]/1 g
INACTIVE INGREDIENTS: LACTOSE 0.985 g/1 g

BM Carbo Veg 3X

Indications: See the leaflet enclosed for detail.

PURPOSE

Indications: See the leaflet enclosed for detail.

DOSAGE AND ADMINISTRATION

Dosage: Adult: Four tablets three times a day, Children: half of the same or as advised by a homoeopathic physician.

WARNINGS

Precautions/storage: Keep away from children and store at cool and dry place.

KEEP OUT OF REACH OF CHILDREN

Precautions/storage: Keep away from children and store at cool and dry place.

STORAGE AND HANDLING

Precautions/storage: Keep away from children and store at cool and dry place.

INACTIVE INGREDIENT

LACTOSE

ACTIVE INGREDIENT

CARBO VEGETABILIS

Entire package label